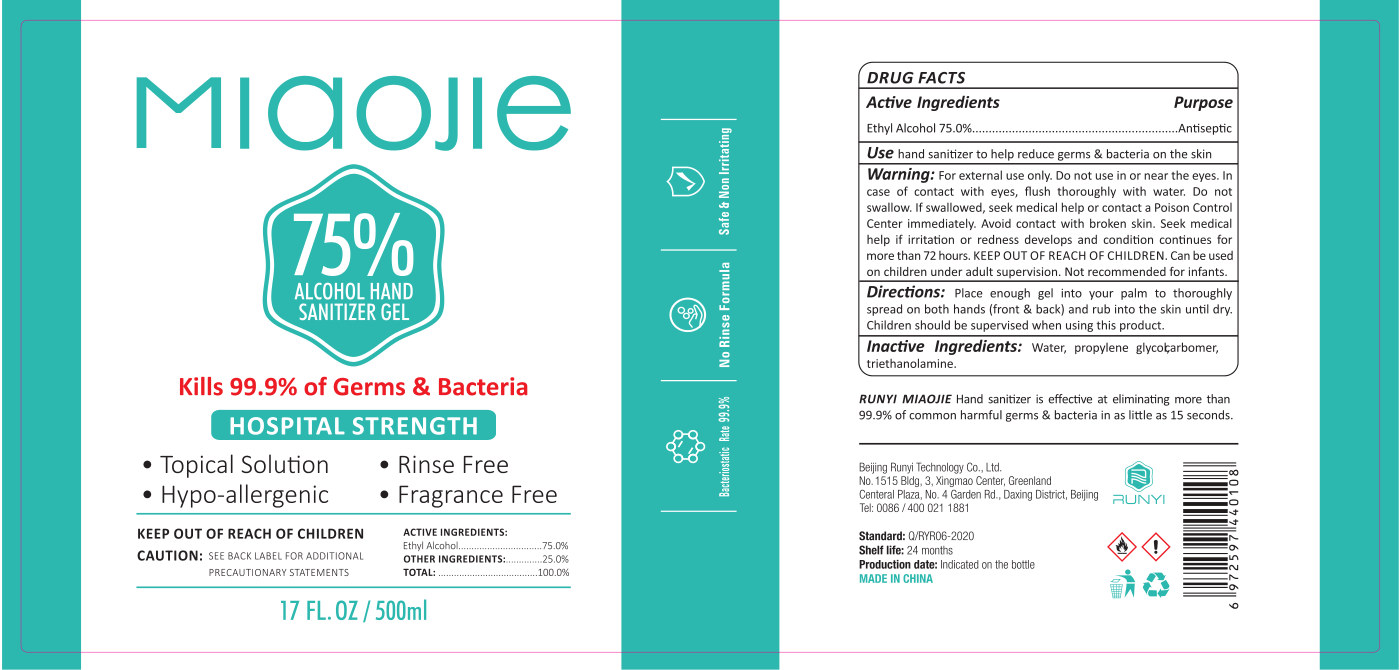 DRUG LABEL: RUNYI MIAOJIE Hand sanitizer
NDC: 41500-013 | Form: GEL
Manufacturer: Beijing Runyi Technology Co., Ltd
Category: otc | Type: HUMAN OTC DRUG LABEL
Date: 20200907

ACTIVE INGREDIENTS: ALCOHOL 375 mL/500 mL
INACTIVE INGREDIENTS: PROPYLENE GLYCOL; WATER; CARBOMER HOMOPOLYMER, UNSPECIFIED TYPE; TROLAMINE

KEEP OUT OF REACH OF CHILDREN SECTION

DOSAGE AND ADMINISTRATION

Store in a cool and dry place

WARNINGS

For external use only.

INACTIVE INGREDIENT

Water、carbomer , triethanolamine , propylene glycol

INDICATIONS AND USAGE

Place enough gel into your palm to thoroughly spread on both hands (front & back) and rub into the skin untl dry.Children should be supervised when using this product.

PURPOSE

Disinfection
Sterilization
No Rinseing

ACTIVE INGREDIENT

ethanol